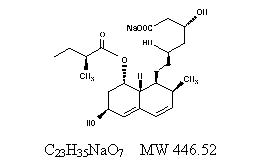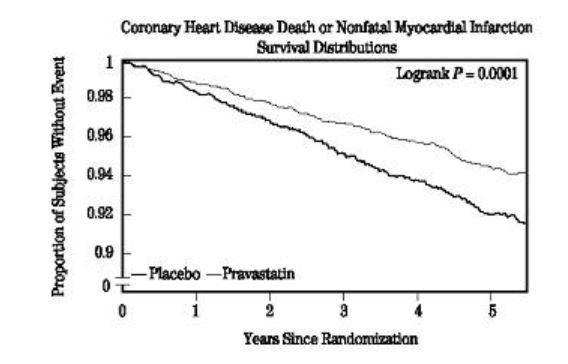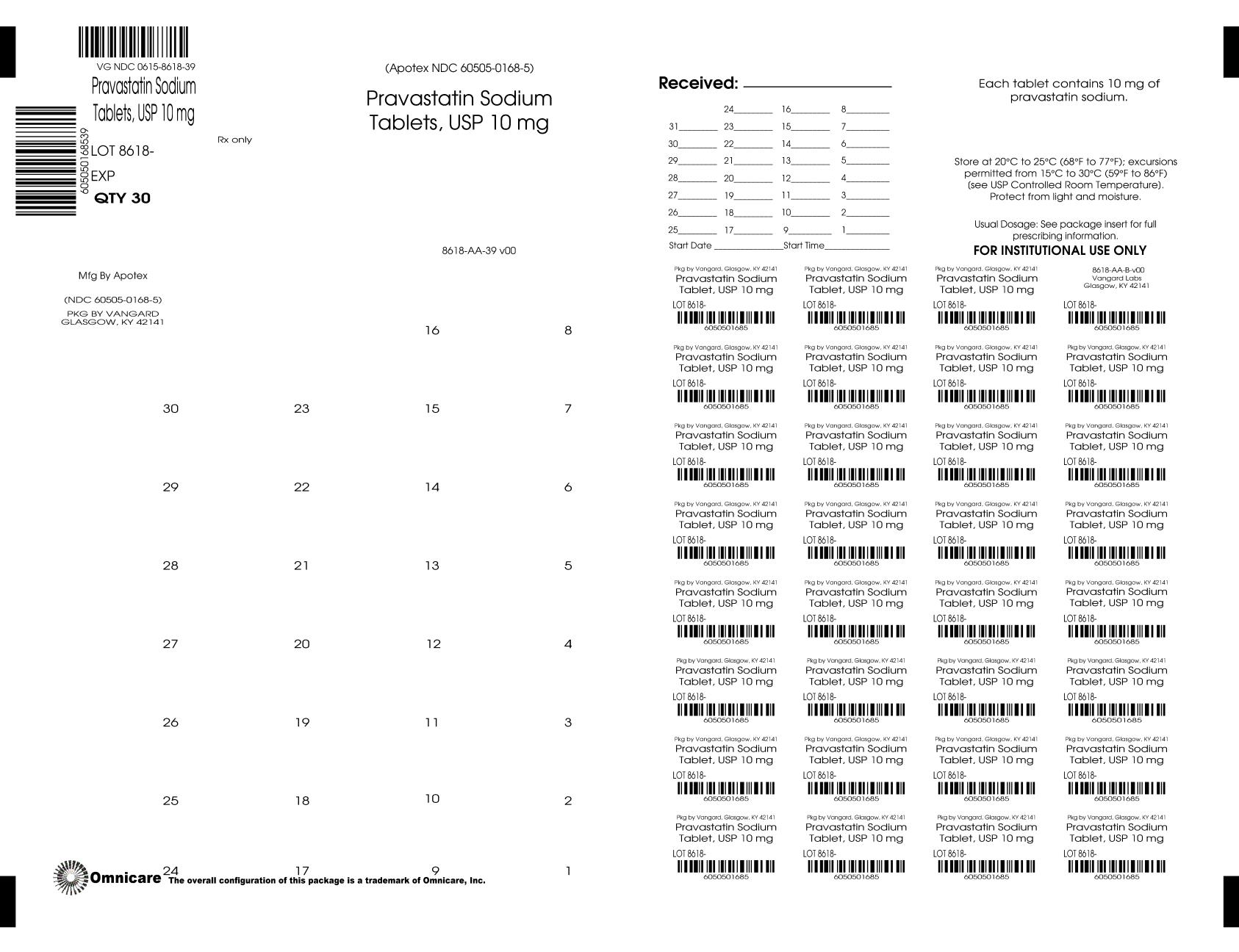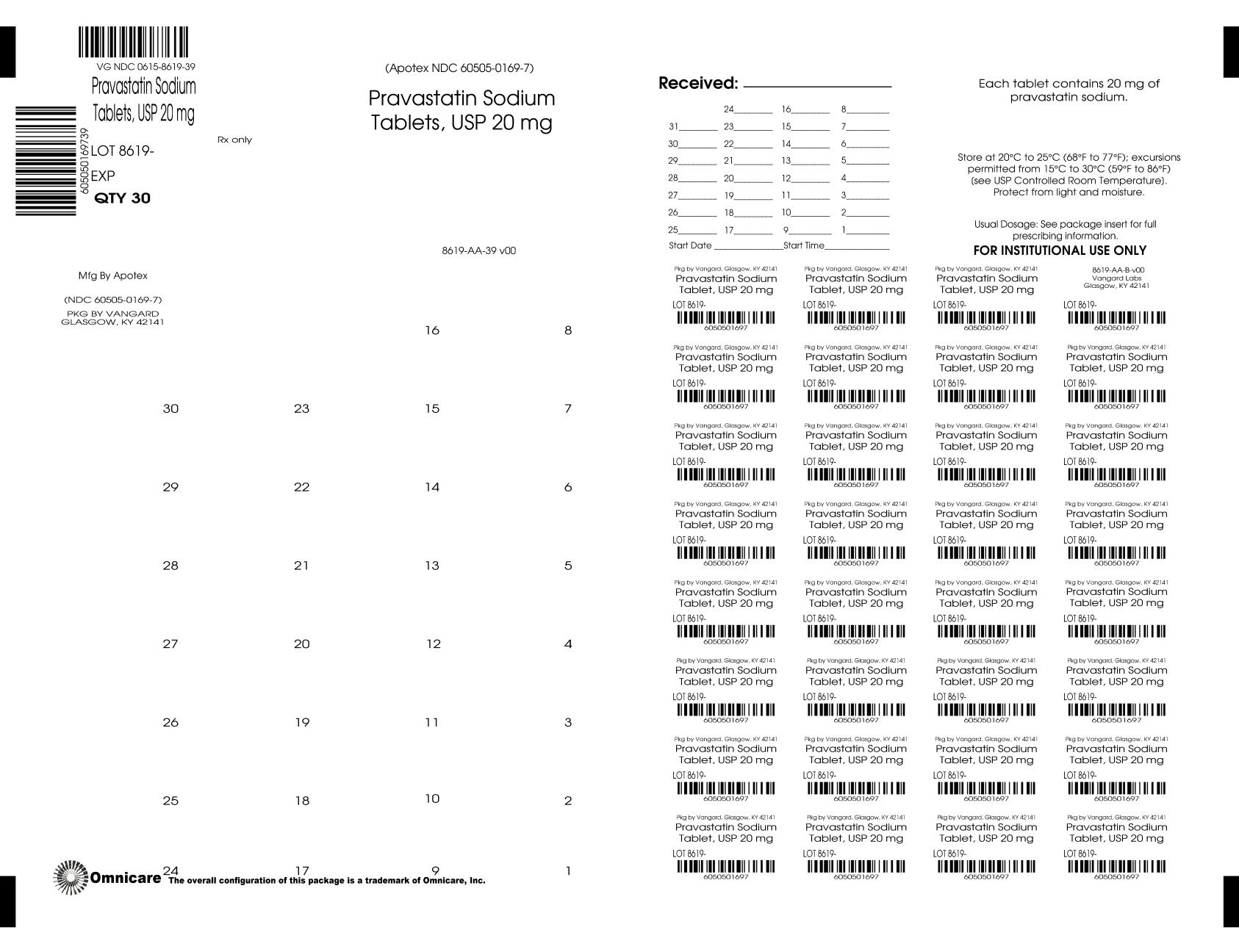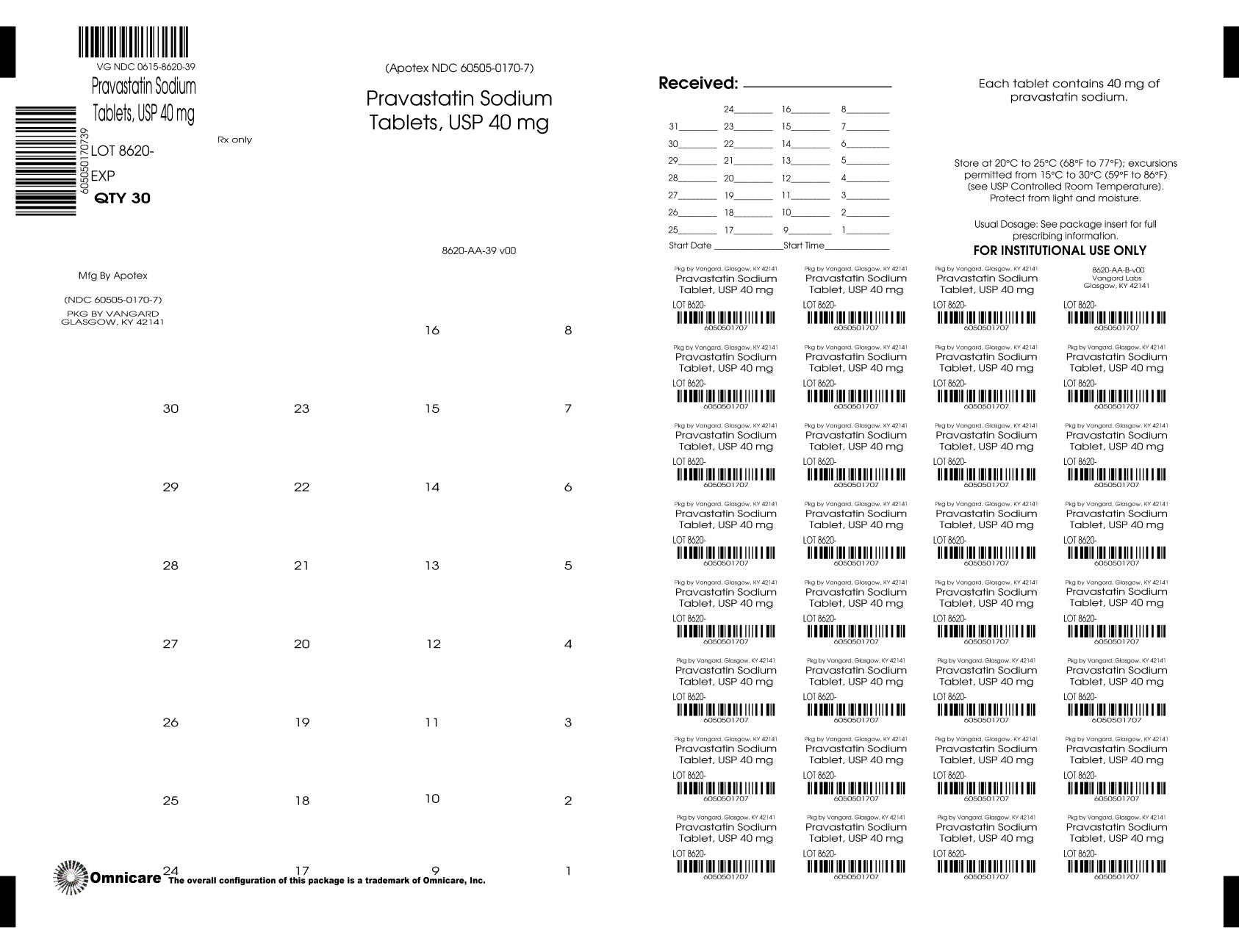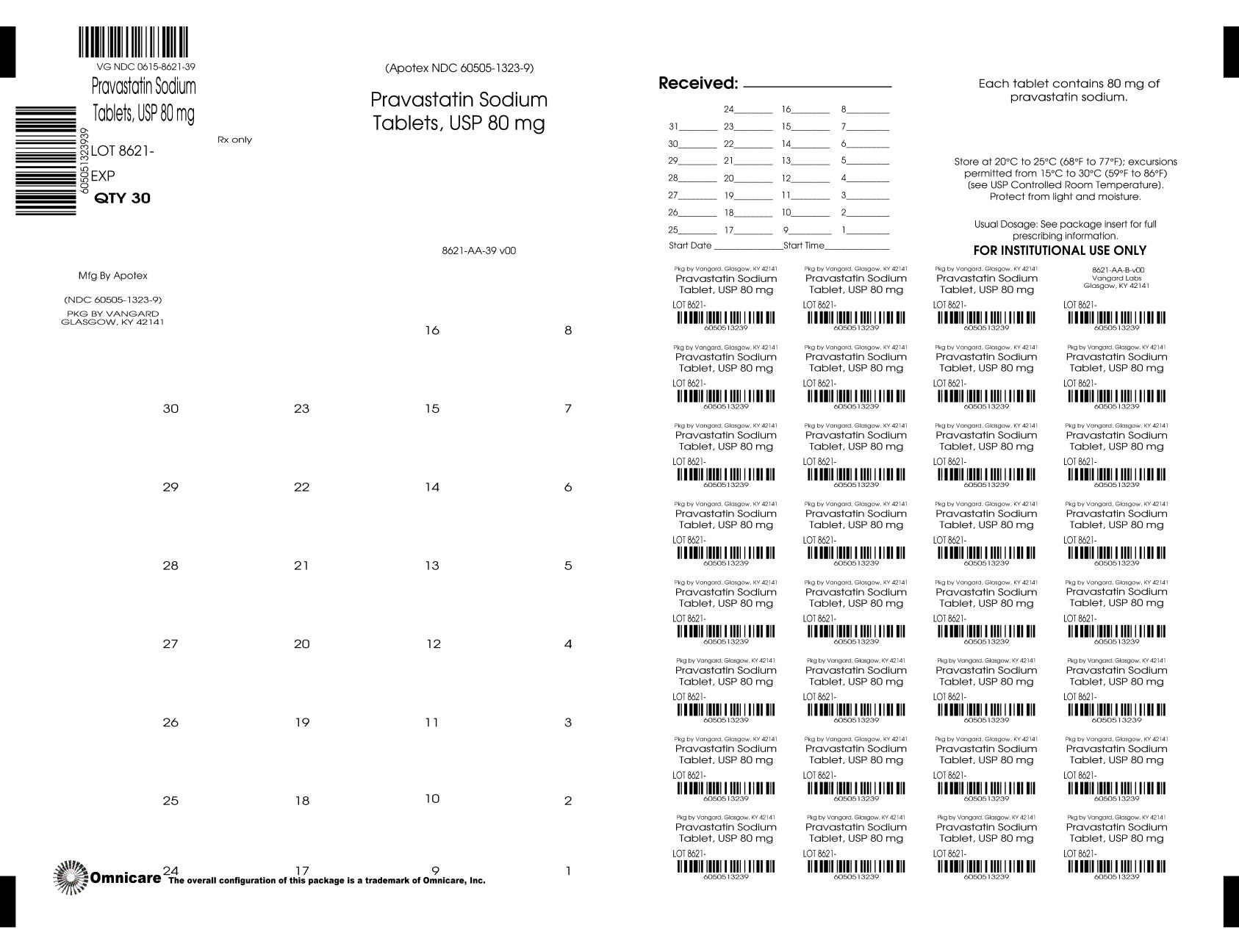 DRUG LABEL: PRAVASTATIN SODIUM
NDC: 0615-8618 | Form: TABLET
Manufacturer: NCS HealthCare of KY, LLC dba Vangard Labs
Category: prescription | Type: HUMAN PRESCRIPTION DRUG LABEL
Date: 20260227

ACTIVE INGREDIENTS: Pravastatin Sodium 10 mg/1 1
INACTIVE INGREDIENTS: CROSCARMELLOSE SODIUM; LACTOSE MONOHYDRATE; MAGNESIUM STEARATE; MICROCRYSTALLINE CELLULOSE; FERRIC OXIDE RED

HIGHLIGHTS OF PRESCRIBING INFORMATION

These highlights do not include all the information needed to use PRAVASTATIN SODIUM TABLETS safely and effectively. See full prescribing information for PRAVASTATIN SODIUM TABLETS.
PRAVASTATIN SODIUM tablets, for oral use
Initial U.S. Approval: 1991

1 INDICATIONS AND USAGE

Pravastatin sodium tablets are an HMG-CoA reductase inhibitor (statin) indicated (1):

- To reduce the risk of myocardial infarction, myocardial revascularization procedures, and cardiovascular mortality in adults with elevated low-density lipoprotein cholesterol (LDL-C) without clinically evident coronary heart disease (CHD).
- To reduce the risk of coronary death, myocardial infarction, myocardial revascularization procedures, stroke or transient ischemic attack, and slow the progression of coronary atherosclerosis in adults with clinically evident CHD.
- As an adjunct to diet to reduce LDL-C in adults with primary hyperlipidemia.
- As an adjunct to diet to reduce LDL-C in pediatric patients ages 8 years and older with heterozygous familial hypercholesterolemia (HeFH).
- As an adjunct to diet for the treatment of adults with:
  - Primary dysbetalipoproteinemia.
  - Hypertriglyceridemia.

2 DOSAGE AND ADMINISTRATION

- Take orally once daily at any time of the day, with or without food (2.1).
- For patients that require a high-intensity statin or are unable to achieve their LDL-C goal receiving pravastatin sodium tablets 80 mg daily, prescribe alternative LDL-C-lowering treatment (2.1).
- Assess LDL-C when clinically appropriate, as early as 4 weeks after initiating pravastatin sodium tablets, and adjust the dosage if necessary (2.1).
- Adults: recommended starting dosage is pravastatin sodium tablets 40 mg to 80 mg once daily. (2.2)
- Pediatric Patients (2.3):
  - aged 8 to 13 years, the recommended dosage is 20 mg once daily.
  - aged 14 to 18 years, the recommended starting dosage is 40 mg once daily.
- Severe renal impairment: recommended starting dosage is pravastatin sodium 10 mg once daily. Use another pravastatin sodium product to initiate dosing. Recommended maximum pravastatin sodium tablets dosage is 40 mg once daily. (2.4)
- See full prescribing information for dosage modifications due to drug interactions (2.5, 7).

3 DOSAGE FORMS AND STRENGTHS

- Tablets: 10 mg, 20 mg, 40 mg, 80 mg. (3)

4 CONTRAINDICATIONS

- Hypersensitivity to pravastatin or any excipient in pravastatin sodium tablets (4)
- Acute liver failure or decompensated cirrhosis (4, 5.3)

5 WARNINGS AND PRECAUTIONS

- Myopathy and Rhabdomyolysis: Risk factors include age 65 years or greater, uncontrolled hypothyroidism, renal impairment, concomitant use with certain other drugs, and higher pravastatin dosage. Discontinue pravastatin if markedly elevated CK levels occur or myopathy is diagnosed or suspected. Temporarily discontinue pravastatin in patients experiencing an acute or serious condition at high risk of developing renal failure secondary to rhabdomyolysis. Inform patients of the risk of myopathy and rhabdomyolysis when starting or increasing pravastatin dosage. Instruct patients to promptly report unexplained muscle pain, tenderness, or weakness, particularly if accompanied by malaise or fever. (5.1, 7.1, 8.5, 8.6)
- Immune-Mediated Necrotizing Myopathy (IMNM): Rare reports of IMNM, an autoimmune myopathy, have been reported. Discontinue pravastatin if IMNM is suspected (5.2).
- Hepatic Dysfunction: Increases in serum transaminases have occurred, some persistent. Rare reports of fatal and non-fatal hepatic failure have occurred. Consider testing liver enzymes before initiating therapy and as clinically indicated thereafter. If serious hepatic injury with clinical symptoms and/or hyperbilirubinemia or jaundice occurs, promptly discontinue (5.3).

6 ADVERSE REACTIONS

In short-term clinical trials, the most commonly reported adverse reactions (≥2% and greater than placebo) were: musculoskeletal pain, nausea/vomiting, upper respiratory infection, diarrhea, and headache. (6.1)

To report SUSPECTED ADVERSE REACTIONS, contact Apotex at 1-800-706-5575 or FDA at 1-800-FDA-1088 or www.fda.gov/medwatch.

7 DRUG INTERACTIONS

- See full prescribing information for details regarding concomitant use of pravastatin sodium tablets with other drugs that increase the risk of myopathy and rhabdomyolysis. (2.5, 7.1)
- Bile Acid Sequestrants: in patients taking a bile acid sequestrant, administer pravastatin sodium tablets at least 1 hour before or at least 4 hours after the bile acid sequestrant (7.2)

8 USE IN SPECIFIC POPULATIONS

- Pregnancy: May cause fetal harm (8.1)
- Lactation: Breastfeeding not recommended during treatment with pravastatin sodium tablets (8.2)

FULL PRESCRIBING INFORMATION

1 INDICATIONS AND USAGE

Pravastatin sodium tablets are indicated:

- To reduce the risk of myocardial infarction, myocardial revascularization procedures, and cardiovascular mortality in adults with elevated low-density lipoprotein cholesterol (LDL-C) without clinically evident coronary heart disease (CHD).
- To reduce the risk of coronary death, myocardial infarction, myocardial revascularization procedures, stroke or transient ischemic attack, and slow the progression of coronary atherosclerosis in adults with clinically evident CHD.
- As an adjunct to diet to reduce LDL-C in adults with primary hyperlipidemia.
- As an adjunct to diet to reduce LDL-C in pediatric patients ages 8 years and older with heterozygous familial hypercholesterolemia (HeFH).
- As an adjunct to diet for the treatment of adults with:
  - Primary dysbetalipoproteinemia.
  - Hypertriglyceridemia.

2 DOSAGE AND ADMINISTRATION

2.1 Important Dosage and Administration Information

- Take pravastatin sodium tablets orally once daily as a single dose at any time of the day, with or without food.
- For patients that require a high-intensity statin or are unable to achieve their LDL-C goal receiving pravastatin sodium tablets 80 mg daily, prescribe alternative LDL-C-lowering treatment.
- Assess LDL-C when clinically appropriate, as early as 4 weeks after initiating pravastatin sodium tablets, and adjust the dosage if necessary.

2.2 Recommended Dosage in Adult Patients

The recommended starting dosage is pravastatin sodium tablets 40 mg to 80 mg once daily.

2.3 Recommended Dosage in Pediatric Patients 8 Years of Age and Older with HeFH

- In pediatric patients aged 8 to 13 years, the recommended dosage is pravastatin sodium tablets 20 mg once daily.
- In pediatric patients aged 14 to 18 years, the recommended starting dosage is pravastatin sodium tablets 40 mg once daily.

2.4 Recommended Dosage in Patients with Renal Impairment

- In patients with severe renal impairment, the recommended starting dosage is pravastatin sodium 10 mg once daily. The maximum recommended dosage of pravastatin sodium tablets in patients with severe renal impairment is 40 mg once daily [see Clinical Pharmacology (12.3)].

- The recommended dosage of pravastatin sodium tablets for patients with mild or moderate renal impairment is the same as patients with normal renal function.

2.5 Dosage and Administration Modifications Due to Drug Interactions

- In patients taking a bile acid sequestrant, administer pravastatin sodium tablets at least 1 hour before or 4 hours after the bile acid sequestrant [see Drug Interactions (7.2)].
- Concomitant use of pravastatin sodium tablets with the following drugs requires dosage modifications of pravastatin sodium tablets [see Warnings and Precautions (5.1) and Drug Interactions (7.1)]:
  - Cyclosporine
  In patients taking cyclosporine, the recommended starting dosage is pravastatin sodium 10 mg once daily. The maximum recommended dosage of pravastatin sodium tablets in patients taking cyclosporine is 20 mg once daily.
  - Clarithromycin and Erythromycin
  The maximum recommended dosage is pravastatin sodium tablets 40 mg once daily.

3 DOSAGE FORMS AND STRENGTHS

Pravastatin Sodium Tablets, USP are supplied as:

10 mg tablets: Light pink, round, unscored tablets, imprinted “APO” on one side and “PRA” over “10” on the other side.

20 mg tablets: Off-white to light yellow, round, unscored tablets, imprinted “APO” on one side and “PRA” over “20” on the other side.

40 mg tablets: Light green, round, unscored tablets, imprinted “APO” on one side and “PRA” over “40” on the other side.

80 mg tablets: Off-white to light yellow, round, unscored tablets, imprinted “APO” on one side and “PRA” over “80” on the other side.

4 CONTRAINDICATIONS

- Acute liver failure or decompensated cirrhosis [see Warnings and Precautions (5.3)].
- Hypersensitivity to any pravastatin or any excipients in pravastatin sodium tablets.

5 WARNINGS AND PRECAUTIONS

5.1 Myopathy and Rhabdomyolysis

Pravastatin may cause myopathy and rhabdomyolysis. Acute kidney injury secondary to myoglobinuria and rare fatalities have occurred as a result of rhabdomyolysis in patients treated with statins, including pravastatin. Myopathy, defined as muscle aching or muscle weakness in conjunction with increases in creatine phosphokinase (CK) to greater than 10 times the upper limit of normal (ULN), occurred <0.1% in pravastatin-treated patients in clinical trials.

Risk Factors for Myopathy

Risk factors for myopathy include age 65 years or greater, uncontrolled hypothyroidism, renal impairment, concomitant use with certain other drugs (including other lipid-lowering therapies), and higher pravastatin dosage [see Drug Interactions (7.1)].

Steps to Prevent or Reduce the Risk of Myopathy and Rhabdomyolysis

Pravastatin is not recommended in patients taking gemfibrozil [see Drug Interactions (7)]. There are pravastatin dosage restrictions for patients taking cyclosporin and select macrolide antibiotics [see Dosage and Administration (2.5)]. The following drugs when used concomitantly with pravastatin may also increase the risk of myopathy and rhabdomyolysis: niacin, fibrates, and colchicine [see Drug Interactions (7)].

Discontinue pravastatin if markedly elevated CK levels occur or myopathy is diagnosed or suspected. Muscle symptoms and CK increases may resolve if pravastatin is discontinued. Temporarily discontinue pravastatin in patients experiencing an acute or serious condition at high risk of developing renal failure secondary to rhabdomyolysis, e.g., sepsis; shock; severe hypovolemia; major surgery; trauma; severe metabolic, endocrine, or electrolyte disorders; or uncontrolled epilepsy.

Inform patients of the risk of myopathy and rhabdomyolysis when starting or increasing the pravastatin dosage. Instruct patients to promptly report any unexplained muscle pain, tenderness or weakness, particularly if accompanied by malaise or fever.

5.2 Immune-Mediated Necrotizing Myopathy

There have been rare reports of immune-mediated necrotizing myopathy (IMNM), an autoimmune myopathy, associated with statin use, including reports of recurrence when the same or a different statin was administered. IMNM is characterized by proximal muscle weakness and elevated serum creatine kinase that persist despite discontinuation of statin treatment; positive anti-HMG CoA reductase antibody; muscle biopsy showing necrotizing myopathy; and improvement with immunosuppressive agents. Additional neuromuscular and serologic testing may be necessary. Treatment with immunosuppressive agents may be required. Discontinue pravastatin if IMNM is suspected.

5.3 Hepatic Dysfunction

Increases in serum transaminases have been reported with use of pravastatin [see Adverse Reactions (6.1)]. In most cases, these changes appeared soon after initiation, were transient, were not accompanied by symptoms, and resolved or improved on continued therapy or after a brief interruption in therapy. Persistent increases to more than three times the ULN in serum transaminases have occurred in approximately 1% of patients receiving either pravastatin or placebo in clinical studies. Marked persistent increases of hepatic transaminases have also occurred with pravastatin. There have been rare postmarketing reports of fatal and non-fatal hepatic failure in patients taking statins, including pravastatin.

Patients who consume substantial quantities of alcohol and/or have a history of liver disease may be at increased risk for hepatic injury.

Consider liver enzyme testing before pravastatin initiation and when clinically indicated thereafter. Pravastatin is contraindicated in patients with acute liver failure or decompensated cirrhosis [see Contraindications (4)]. If serious hepatic injury with clinical symptoms and/or hyperbilirubinemia or jaundice occurs, promptly discontinue pravastatin.

5.4 Increases in HbA1c and Fasting Serum Glucose Levels

Increases in HbA1c and fasting serum glucose levels have been reported with statins, including pravastatin. Optimize lifestyle measures, including regular exercise, maintaining a healthy body weight, and making healthy food choices.

6 ADVERSE REACTIONS

The following important adverse reactions are described below and elsewhere in the labeling:

- Myopathy and Rhabdomyolysis [see Warnings and Precautions (5.1)]
- Immune-Mediated Necrotizing Myopathy [see Warnings and Precautions (5.2)]
- Hepatic Dysfunction [see Warnings and Precautions (5.3)]
- Increases in HbA1c and Fasting Serum Glucose Levels [see Warnings and Precautions (5.4)]

6.1 Clinical Trials Experience

Because clinical studies are conducted under widely varying conditions, adverse reaction rates observed in the clinical studies of a drug cannot be directly compared to rates in the clinical studies of another drug and may not reflect the rates observed in practice.

In pravastatin placebo-controlled clinical trials, 1,313 patients (age range 20 to 76 years, 32% women, 93.5% White, 5% Black, 0.9% Hispanic, 0.4% Asian, 0.2% Other) with a median treatment duration of 14 weeks, 3.3% of patients on pravastatin and 1.2% patients on placebo discontinued due to adverse reactions (regardless of causality). The most common adverse reactions that led to treatment discontinuation and occurred at an incidence greater than placebo were: hepatic transaminase elevations, nausea, anxiety/depression, and dizziness.

Adverse reactions (regardless of causality) reported in ≥2% of pravastatin-treated patients in placebo-controlled trials of up to 8 months duration are identified in Table 1:

Table 1: Adverse Reactions in ≥ 2% of Patients Treated with Pravastatin (Any Dose) and at an Incidence Greater Than Placebo in Short-Term Placebo-Controlled Trials

 | % Placebo N=411 | % Any Dose N=902
Nausea/Vomiting | 7.1 | 7.4
Diarrhea | 5.6 | 6.7
Headache | 4.6 | 6.3
Upper Respiratory Infection | 5.8 | 5.9
Angina Pectoris | 3.4 | 4.5
Rash | 1.4 | 4.5
CPK Increased | 3.6 | 4.1
Dizziness | 3.4 | 3.5
ALT Increased | 1.2 | 2.9
Chest Pain | 1.9 | 2.7
Cough | 1.7 | 2.5
Myalgia | 1.2 | 2.3
Influenza | 0.7 | 2.0
g-GT Increased | 1.2 | 2.0

Adverse Reactions (regardless of causality)

The safety and tolerability of pravastatin at a dose of 80 mg in 2 controlled trials with a mean exposure of 8.6 months was similar to that of pravastatin at lower doses except that 4 out of 464 patients taking 80 mg of pravastatin had a single elevation of CK >10 times ULN compared to 0 out of 115 patients taking 40 mg of pravastatin.

In pravastatin placebo-controlled clinical trials, 21,483 patients (age range 24 to 75 years, 10.3% women, 52.3% White, 0.8% Black, 0.5% Hispanic, 0.1% Asian, 0.1% Other, 46.1% not recorded) had a median treatment duration of 261 weeks.

Adverse reactions (regardless of causality) were pooled from 7 double-blind, placebo-controlled trials (West of Scotland Coronary Prevention Study [WOS]; Cholesterol and Recurrent Events study [CARE]; Long-term Intervention with Pravastatin in Ischemic Disease study [LIPID]; Pravastatin Limitation of Atherosclerosis in the Coronary Arteries study [PLAC I]; Pravastatin, Lipids and Atherosclerosis in the Carotids study [PLAC II]; Regression Growth Evaluation Statin Study [REGRESS]; and Kuopio Atherosclerosis Prevention Study [KAPS]) involving a total of 10,764 patients treated with pravastatin 40 mg and 10,719 patients treated with placebo. Patients were exposed to pravastatin for a mean of 4 to 5.1 years in WOS, CARE, and LIPID and 1.9 to 2.9 years in PLAC I, PLAC II, KAPS, and REGRESS. Adverse reactions (regardless of causality) occurring in ≥5% of patients treated with pravastatin in these studies are identified in Table 2:

Table 2: Adverse Reactions in ≥ 5% of Patients Treated with Pravastatin 40 mg and at an Incidence Greater than Placebo in Long-Term Placebo-Controlled Trials

 | Placebo (N=10,719) % of patients | Pravastatin (N=10,764) % of patients
Musculoskeletal Pain | 24.4 | 24.9
Upper Respiratory Tract Infection | 20.2 | 21.2
Musculoskeletal Traumatism | 9.6 | 10.2
Chest Pain | 9.8 | 10.0
Influenza | 9.0 | 9.2
Fatigue | 7.8 | 8.4
Cough | 7.4 | 8.2
Dizziness | 6.6 | 7.3
Rash (including dermatitis) | 7.1 | 7.2
Sinus Abnormality | 6.7 | 7.0
Muscle Cramp | 4.6 | 5.1

Adverse Reactions (regardless of causality)

No new adverse reactions were identified in a study of pediatric patients with HeFH.

Laboratory Abnormalities

Increases in ALT, AST values and CK have been observed.

Transient, asymptomatic eosinophilia has been reported. Eosinophil counts usually returned to normal despite continued therapy. Anemia, thrombocytopenia, and leukopenia have been reported with statins.

6.2 Postmarketing Experience

The following adverse reactions have been identified during postapproval use of pravastatin.

Because these reactions are reported voluntarily from a population of uncertain size, it is not always possible to reliably estimate their frequency or establish a causal relationship to drug exposure.

Musculoskeletal: myopathy, rhabdomyolysis, tendon disorder, polymyositis, immune-mediated necrotizing myopathy associated with statin use.

Nervous System: dysfunction of certain cranial nerves (including alteration of taste, impairment of extraocular movement, facial paresis), peripheral nerve palsy. Rare postmarketing reports of cognitive impairment (e.g., memory loss, forgetfulness, amnesia, memory impairment, confusion) associated with statin use. Cognitive impairment was generally nonserious, and reversible upon statin discontinuation, with variable times to symptom onset (1 day to years) and symptom resolution (median of 3 weeks).

There have been rare reports of new-onset or exacerbation of myasthenia gravis, including ocular myasthenia, and reports of recurrence when the same or a different statin was administered.

Hypersensitivity: anaphylaxis, angioedema, lupus erythematosus-like syndrome, polymyalgia rheumatica, dermatomyositis, vasculitis, purpura, hemolytic anemia, positive ANA, ESR increase, arthritis, arthralgia, asthenia, photosensitivity, chills, malaise, toxic epidermal necrolysis, erythema multiforme (including Stevens-Johnson syndrome).

Gastrointestinal: abdominal pain, constipation, pancreatitis, hepatitis (including chronic active hepatitis), cholestatic jaundice, fatty change in liver, cirrhosis, fulminant hepatic necrosis, hepatoma, fatal and non-fatal hepatic failure.

Dermatologic: a variety of skin changes (e.g., nodules, discoloration, dryness of mucous membranes, changes to hair/nails), lichen planus.

Renal: urinary abnormality (including dysuria, frequency, nocturia).

Respiratory: dyspnea, interstitial lung disease.

Psychiatric: nightmare.

Reproductive: gynecomastia.

Laboratory Abnormalities: liver function test abnormalities, thyroid function abnormalities.

7 DRUG INTERACTIONS

7.1 Drug Interactions that Increase the Risk of Myopathy and Rhabdomyolysis with Pravastatin

Pravastatin is a substrate of the transport protein OATP1B1. Pravastatin plasma levels can be significantly increased with concomitant administration of inhibitors of OATP1B1. Table 3 includes a list of drugs that increase the risk of myopathy and rhabdomyolysis when used concomitantly with pravastatin and instructions for preventing or managing them [see Warnings and Precautions (5.1) and Clinical Pharmacology (12.3)].

Table 3: Drug Interactions that Increase the Risk of Myopathy and Rhabdomyolysis with Pravastatin

Gemfibrozil
Clinical Impact: | There is an increased risk of myopathy/rhabdomyolysis when pravastatin is administered with gemfibrozil
Intervention: | Avoid concomitant use of gemfibrozil with pravastatin .
Cyclosporine
Clinical Impact: | The risk of myopathy and rhabdomyolysis is increased with concomitant use of cyclosporine with pravastatin.
Intervention: | Initiate with a dosage of pravastatin sodium 10 mg once daily. Do not exceed pravastatin 20 mg once daily [see Dosage and Administration (2.5)].
Select Macrolide Antibiotics
Clinical Impact: | The risk of myopathy and rhabdomyolysis is increased by concomitant use of clarithromycin or erythromycin with pravastatin. Other macrolides (e.g., azithromycin) have the potential to increase pravastatin exposures and increase the risk of myopathy and rhabdomyolysis when used concomintantly.
Intervention: | For patients taking erythromycin or clarithromycin, do not exceed 40 mg pravastatin once daily [see Dosage and Administration (2.5)].
Niacin
Clinical Impact: | Cases of myopathy and rhabdomyolysis have been observed with concomitant use of niacin with pravastatin.
Intervention: | Consider if the benefit of using niacin concomitantly with pravastatin outweighs the increased risk of myopathy and rhabdomyolysis. If concomitant use is decided, monitor patients for signs and symptoms of myopathy, particularly during initiation of therapy and during upward dose titration of either drug.
Fibrates (other than Gemfibrozil)
Clinical Impact: | Fibrates may cause myopathy when given alone. The risk of myopathy and rhabdomyolysis is increased with concomitant use of fibrates with pravastatin.
Intervention: | Consider if the benefit of using fibrates concomitantly with pravastatin outweighs the increased risk of myopathy and rhabdomyolysis. If concomitant use is decided, monitor patients for signs and symptoms of myopathy, particularly during initiation of therapy and during upward dose titration of either drug.
Colchicine
Clinical Impact: | Cases of myopathy and rhabdomyolysis have been reported with concomitant use of colchicine with pravastatin.
Intervention: | Consider if the benefit of using colchicine concomitantly with pravastatin outweighs the increased risk of myopathy and rhabdomyolysis. If concomitant use is decided, monitor patients for signs and symptoms of myopathy, particularly during initiation of therapy and during upward dose titration of either drug.

7.2 Drug Interactions that Decrease the Efficacy of Pravastatin

Table 4 presents drug interactions that may decrease the efficacy of pravastatin and instructions for preventing or managing them.

Table 4: Drug Interactions that Decrease the Efficacy of Pravastatin

Bile Acid Sequestrants
Clinical Impact: | Concomitant cholestyramine or colestipol administration decreased the mean exposure of pravastatin approximately 51% and 47%, respectively [see Clinical Pharmacology (12.3)].
Intervention: | In patients taking a bile acid sequestrant, administer pravastatin at least 1 hour before or at least 4 hours after the bile acid sequestrant [see Dosage and Administration (2.5)].

8 USE IN SPECIFIC POPULATIONS

8.1 Pregnancy

Risk Summary

Discontinue pravastatin when pregnancy is recognized. Alternatively, consider the ongoing therapeutic needs of the individual patient. Pravastatin decreases synthesis of cholesterol and possibly other biologically active substances derived from cholesterol; therefore, pravastatin may cause fetal harm when administered to pregnant patients based on the mechanism of action [see Clinical Pharmacology (12.1)]. In addition, treatment of hyperlipidemia is not generally necessary during pregnancy. Atherosclerosis is a chronic process and the discontinuation of lipid-lowering drugs during pregnancy should have little impact on the outcome of long-term therapy of primary hyperlipidemia for most patients. Available data from case series and prospective and retrospective observational cohort studies over decades of use with statins in pregnant women have not identified a drug-associated risk of major congenital malformations. Published data from prospective and retrospective observational cohort studies with pravastatin use in pregnant women are insufficient to determine if there is a drug-associated risk of miscarriage (see Data). In animal reproduction studies, no evidence of fetal malformations was seen in pregnant rats or rabbits orally administered pravastatin during the period of organogenesis at doses that resulted in 10 times and 120 times, respectively, the human exposure at the maximum recommended human dose (MRHD) of 80 mg/day, based on body surface area (mg/m^2). An imbalance in some fetal skeletal variations, increased offspring mortality, and developmental delays occurred when pregnant rats were exposed to 10 times to 12 times the MRHD during organogenesis to parturition (see Data).

The estimated background risk of major birth defects and miscarriage for the indicated population is unknown. In the U.S. general population, the estimated background risk of major birth defects and miscarriage in clinically recognized pregnancies is 2% to 4% and 15% to 20%, respectively.

Data

Human Data

A Medicaid cohort linkage study of 1,152 statin-exposed pregnant women compared to 886,996 controls did not find a significant teratogenic effect from maternal use of statins in the first trimester of pregnancy, after adjusting for potential cofounders – including maternal age, diabetes mellitus, hypertension, obesity, and alcohol and tobacco use – using propensity score-based methods. The relative risk of congenital malformations between the group with statin use and the group with no statin use in the first trimester was 1.07 (95% confidence interval 0.85 to 1.37) after controlling for confounders, particularly pre-existing diabetes mellitus. There were also no statistically significant increases in any of the organ-specific malformations assessed after accounting for cofounders. In the majority of pregnancies, statin treatment was initiated prior to pregnancy and was discontinued at some point in the first trimester when pregnancy was identified. Study limitations include reliance on physician coding to define the presence of a malformation, lack of control for certain confounders such as body mass index, use of prescription dispensing as verification for the use of a statin, and lack of information on non-live births.

Animal Data

Embryofetal and neonatal mortality was observed in rats given pravastatin during the period of organogenesis or during organogenesis continuing through weaning. In pregnant rats given oral gavage doses of 4 mg/kg/day, 20 mg/kg/day, 100 mg/kg/day, 500 mg/kg/day, and 1,000 mg/kg/day from gestation days 7 through 17 (organogenesis) increased mortality of offspring and increased cervical rib skeletal anomalies were observed at ≥100 mg/kg/day systemic exposure, 10 times the human exposure at 80 mg/day MRHD based on body surface area (mg/m^2).

In other studies, no teratogenic effects were observed when pravastatin was dosed orally during organogenesis in rabbits (gestation days 6 through 18) up to 50 mg/kg/day or in rats (gestation days 7 through 17) up to 1,000 mg/kg/day. Exposures were 10 times (rabbit) or 120 times (rat) the human exposure at 80 mg/day MRHD based on body surface area (mg/m^2).

In pregnant rats given oral gavage doses of 10 mg/kg/day, 100 mg/kg/day, and 1,000 mg/kg/day from gestation day 17 through lactation day 21 (weaning), developmental delays were observed at ≥100 mg/kg/day systemic exposure, corresponding to 12 times the human exposure at 80 mg/day MRHD, based on body surface area (mg/m^2).

In pregnant rats, pravastatin crosses the placenta and is found in fetal tissue at 30% of the maternal plasma levels following administration of a single dose of 20 mg/day orally on gestation day 18, which corresponds to exposure 2 times the MRHD of 80 mg daily based on body surface area (mg/m^2).

8.2 Lactation

Risk Summary

Based on one lactation study in published literature, pravastatin is present in human milk. There is no available information on the effects of the drug on the breastfed infant or the effects of the drug on milk production. Statins, including pravastatin, decrease cholesterol synthesis and possibly the synthesis of other biologically active substances derived from cholesterol and may cause harm to the breastfed infant.

Because of the potential for serious adverse reactions in a breastfed infant, based on the mechanism of action, advise patients that breastfeeding is not recommended during treatment with pravastatin [see Use in Specific Populations (8.1), Clinical Pharmacology (12.1)].

8.4 Pediatric Use

The safety and effectiveness of pravastatin as an adjunct to diet to reduce LDL-C have been established in pediatric patients 8 years of age and older with HeFH. Use of pravastatin for this indication is based on a double-blind, placebo-controlled clinical study in 214 pediatric patients (100 males and 114 females) 8 years of age and older with HeFH. Doses greater than 40 mg daily have not been studied in this population.

The safety and effectiveness of pravastatin have not been established in pediatric patients younger than 10 years of age with HeFH or in pediatric patients with other types of hyperlipidemia (other than HeFH).

8.5 Geriatric Use

In clinical studies, 4,797 (36.4%) pravastatin-treated patients were aged 65 and older and 110 (0.8%) were aged 75 and older. No significant differences in efficacy or safety were observed between geriatric patients and younger patients.

Mean pravastatin AUCs are 25% to 50% higher in elderly subjects than in healthy young subjects, but mean maximum plasma concentration (Cmax), time to maximum plasma concentration (Tmax), and half-life (t½) values are similar in both age groups and substantial accumulation of pravastatin would not be expected in the elderly [see Clinical Pharmacology (12.3)].

Advanced age (≥65 years) is a risk factor for pravastatin-associated myopathy and rhabdomyolysis. Dose selection for an elderly patient should be cautious, recognizing the greater frequency of decreased hepatic, renal, or cardiac function, and of concomitant disease or other drug therapy and the higher risk of myopathy. Monitor geriatric patients receiving pravastatin for the increased risk of myopathy [see Warnings and Precautions (5.1)].

8.6 Renal Impairment

Renal impairment is a risk factor for myopathy and rhabdomyolysis. Monitor all patients with renal impairment for development of myopathy.

In patients with severe renal impairment, the recommended starting dose is pravastatin sodium 10 mg once daily. The maximum recommended dosage in patients with severe renal impairment is pravastatin 40 mg once daily. The recommended dosage for patients with mild or moderate renal impairment is the same as patients with normal renal function [see Dosage and Administration (2.4), Warnings and Precautions (5.1), Clinical Pharmacology (12.3)].

8.7 Hepatic Impairment

Pravastatin shows a large inter-subject variability in pharmacokinetics in patients with liver cirrhosis [Clinical Pharmacology (12.3)]. Pravastatin is contraindicated in patients with acute liver failure or decompensated cirrhosis [see Contraindications (4), Warnings and Precautions (5.3)].

10 OVERDOSAGE

No specific antidotes for pravastatin are known. Contact Poison Control (1-800-222-1222) for latest recommendations.

11 DESCRIPTION

Pravastatin sodium is a statin, an inhibitor of 3-hydroxy-3-methylglutaryl-coenzyme A (HMG-CoA) reductase.

Pravastatin sodium is designated chemically as Sodium (3R,5R)-3,5-dihydroxy-7-[(1S,2S,6S,8S,8aR)-6-hydroxy-2-methyl-8-[[(2S)-methylbutanoyl]oxy]-1,2,6,7,8,8a-hexahydronaphthalen-1-yl]heptanoate.

Structural Formula:

Pravastatin sodium is an odorless, white to off-white, fine or crystalline powder. It is a relatively polar hydrophilic compound with a partition coefficient (octanol/ water) of 0.59 at a pH of 7. It is soluble in methanol and water (>300 mg/mL), slightly soluble in isopropanol, and practically insoluble in acetone, acetonitrile, chloroform, and ether.

Pravastatin sodium tablets for oral use contains 10 mg, 20 mg, 40 mg and 80mg pravastatin sodium. Inactive ingredients include: croscarmellose sodium, lactose monohydrate, magnesium stearate and microcrystalline cellulose. The 10 mg tablet also contains Red Ferric Oxide, the 20 mg tablet also contains Yellow Ferric Oxide, the 40 mg tablet also contains a blend of Yellow Ferric Oxide and FD&C Blue #1 Aluminum Lake, and the 80 mg tablet also contains Yellow Ferric Oxide.

12 CLINICAL PHARMACOLOGY

12.1 Mechanism of Action

Pravastatin is a reversible inhibitor of HMG-CoA reductase, the rate-limiting enzyme that converts HMG-CoA to mevalonate, a precursor of cholesterol.

12.2 Pharmacodynamics

Inhibition of HMG-CoA reductase by pravastatin accelerates the expression of LDL-receptors, followed by the uptake of LDL-C from blood to the liver, leading to a decrease in plasma LDL-C and total cholesterol. Sustained inhibition of cholesterol synthesis in the liver also decreases levels of very-low-density lipoproteins. The maximum LDL-C reduction of pravastatin is usually achieved by 4 weeks and is maintained after that.

12.3 Pharmacokinetics

Absorption

Pravastatin is administered orally in the active form. Peak plasma pravastatin concentrations occurred 1 to 1.5 hours upon oral administration. Based on urinary recovery of total radiolabeled drug, the average oral absorption of pravastatin is 34% and absolute bioavailability is 17%. While the presence of food in the gastrointestinal tract reduces area under the concentration-time curve (AUC) and Cmax by 31% and 49%, respectively, the lipid-lowering effects of the drug are similar whether taken with or 1 hour prior to meals.

Pravastatin plasma concentrations, including AUC, Cmax, and steady-state minimum (Cmin), are directly proportional to administered dose. Systemic bioavailability of pravastatin administered following a bedtime dose was decreased 60% compared to that following an AM dose. Despite this decrease in systemic bioavailability, the efficacy of pravastatin administered once daily in the evening, although not statistically significant, was marginally more effective than that after a morning dose.

The coefficient of variation (CV), based on between-subject variability, was 50% to 60% for AUC. The geometric means of pravastatin Cmax and AUC following a 20 mg dose in the fasted state were 26.5 ng/mL and 59.8 ng*hr/mL, respectively.

Steady-state AUCs, Cmax, and Cmin plasma concentrations showed no evidence of pravastatin accumulation following once or twice daily administration of pravastatin tablets.

Distribution

Approximately 50% of the circulating drug is bound to plasma proteins.

Elimination

Metabolism

The major biotransformation pathways for pravastatin are: (a) isomerization to 6-epi pravastatin and the 3α-hydroxy isomer of pravastatin (SQ 31,906) and (b) enzymatic ring hydroxylation to SQ 31,945. The 3α-hydroxy isomeric metabolite (SQ 31,906) has 1/10 to 1/40 the HMG-CoA reductase inhibitory activity of the parent compound. Pravastatin undergoes extensive first-pass extraction in the liver (extraction ratio 0.66).

Excretion

Approximately 20% of a radiolabeled oral dose is excreted in urine and 70% in the feces. After intravenous administration of radiolabeled pravastatin to normal volunteers, approximately 47% of total body clearance was via renal excretion and 53% by non-renal routes (i.e., biliary excretion and biotransformation).

Following single dose oral administration of ^14C-pravastatin, the radioactive elimination t½ for pravastatin is 1.8 hours in humans and the elimination half-life (t½) for total radioactivity (pravastatin plus metabolites) is 77 hours.

Specific Populations

Renal Impairment

A single 20 mg oral dose of pravastatin was administered to 24 patients with varying degrees of renal impairment (as determined by creatinine clearance). No effect was observed on the pharmacokinetics of pravastatin or its 3α-hydroxy isomeric metabolite (SQ 31,906). Compared to healthy subjects with normal renal function, patients with severe renal impairment had 69% and 37% higher mean AUC and Cmax values, respectively, and a 0.61 hour shorter t½ for the inactive enzymatic ring hydroxylation metabolite (SQ 31,945) [see Use in Specific Populations (8.6)].

Hepatic Impairment

In a study comparing the kinetics of pravastatin in patients with biopsy confirmed cirrhosis (N=7) and normal subjects (N=7), the mean AUC varied 18-fold in cirrhotic patients and 5-fold in healthy subjects. Similarly, the peak pravastatin values varied 47-fold for cirrhotic patients compared to 6-fold for healthy subjects [see Use in Specific Populations (8.6)].

Geriatric

In a single oral dose study using pravastatin 20 mg, the mean AUC for pravastatin was approximately 27% greater and the mean cumulative urinary excretion (CUE) approximately 19% lower in elderly men (65 to 75 years old) compared with younger men (19 to 31 years old). In a similar study conducted in women, the mean AUC for pravastatin was approximately 46% higher and the mean CUE approximately 18% lower in elderly women (65 to 78 years old) compared with younger women (18 to 38 years old). In both studies, Cmax, Tmax, and t½ values were similar in older and younger subjects [see Use in Specific Populations (8.5)].

Pediatric

After 2 weeks of once-daily 20 mg oral pravastatin administration, the geometric means of AUC were 80.7 (CV 44%) and 44.8 (CV 89%) ng*hr/mL for pediatric patients 8 to 11 years (N=14) and 12 to 16 years (N=10), respectively. The corresponding values for Cmax were 42.4 (CV 54%) and 18.6 ng/mL (CV 100%) for pediatric patients 8 to 11 years and 12 to 16 years, respectively. No conclusion can be made based on these findings due to the small number of samples and large variability [see Use in Specific Populations (8.4)].

Drug-Drug Interactions

Table 5: Effect of Coadministered Drugs on the Pharmacokinetics of Pravastatin

Coadministered Drug and Dosing Regimen | Pravastatin
Coadministered Drug and Dosing Regimen | Dose (mg) | Change in AUC | Change in Cmax
Cyclosporine 5 mg/kg single dose | 40 mg single dose | ↑282% | ↑327%
Clarithromycin 500 mg BID for 9 days | 40 mg OD for 8 days | ↑110% | ↑128%
Boceprevir 800 mg TID for 6 days | 40 mg single dose | ↑63% | ↑49%
Darunavir 600 mg BID/Ritonavir 100 mg BID for 7 days | 40 mg single dose | ↑81% | ↑63%
Colestipol 10 g single dose | 20 mg single dose | ↓47% | ↓53%
Cholestyramine 4 g single dose Administered simultaneously Administered 1 hour prior to cholestyramine Administered 4 hours after cholestyramine | 20 mg single dose | ↓40% ↑12% ↓12% | ↓39% ↑30% ↓6.8%
Cholestyramine 24 g OD for 4 weeks | 20 mg BID for 8 weeks 5 mg BID for 8 weeks 10 mg BID for 8 weeks | ↓51% ↓38% ↓18% | ↑4.9% ↑23% ↓33%
Fluconazole 200 mg IV for 6 days 200 mg PO for 6 days | 20 mg PO+10 mg IV 20 mg PO+10 mg IV | ↓34% ↓16% | ↓33% ↓16%
Kaletra 400 mg/100 mg BID for 14 days | 20 mg OD for 4 days | ↑33% | ↑26%
Verapamil IR 120 mg for 1 day and Verapamil ER 480 mg for 3 days | 40 mg single dose | ↑31% | ↑42%
Cimetidine 300 mg QID for 3 days | 20 mg single dose | ↑30% | ↑9.8%
Antacids 15 mL QID for 3 days | 20 mg single dose | ↓28% | ↓24%
Digoxin 0.2 mg OD for 9 days | 20 mg OD for 9 days | ↑23% | ↑26%
Probucol 500 mg single dose | 20 mg single dose | ↑14% | ↑24%
Warfarin 5 mg OD for 6 days | 20 mg BID for 6 days | ↓13% | ↑6.7%
Itraconazole 200 mg OD for 30 days | 40 mg OD for 30 days | ↑11% (compared to Day 1) | ↑17% (compared to Day 1)
Gemfibrozil 600 mg single dose | 20 mg single dose | ↓7.0% | ↓20%
Aspirin 324 mg single dose | 20 mg single dose | ↑4.7% | ↑8.9%
Niacin 1 g single dose | 20 mg single dose | ↓3.6% | ↓8.2%
Diltiazem | 20 mg single dose | ↑2.7% | ↑30%
Grapefruit juice | 40 mg single dose | ↓1.8% | ↑3.7%

BID = twice daily; OD = once daily; QID = four times daily

Table 6: Effect of Pravastatin on the Pharmacokinetics of Coadministered Drugs

Pravastatin Dosing Regimen | Name and Dose | Change in AUC | Change in Cmax
20 mg BID for 6 days | Warfarin 5 mg OD for 6 days Change in mean prothrombin time | ↑17% ↑0.4 sec | ↑15%
20 mg OD for 9 days | Digoxin 0.2 mg OD for 9 days | ↑4.6% | ↑5.3%
20 mg BID for 4 weeks 10 mg BID for 4 weeks 5 mg BID for 4 weeks | Antipyrine 1.2 g single dose | ↑3.0% ↑1.6% ↑Less than 1% | Not Reported
20 mg OD for 4 days | Kaletra 400 mg/100 mg BID for 14 days | No change | No change

BID = twice daily; OD = once daily

13 NONCLINICAL TOXICOLOGY

13.1 Carcinogenesis, Mutagenesis, Impairment of Fertility

In a 2-year study in rats fed pravastatin at doses of 10, 30, or 100 mg/kg body weight, there was an increased incidence of hepatocellular carcinomas in males at the highest dose (p<0.01). These effects in rats were observed at approximately 12 times the human dose (HD) of 80 mg based on body surface area (mg/m^2) and at approximately 4 times the HD, based on AUC.

In a 2-year study in mice fed pravastatin at doses of 250 and 500 mg/kg/day, there was an increased incidence of hepatocellular carcinomas in males and females at both 250 and 500 mg/kg/day (p<0.0001). At these doses, lung adenomas in females were increased (p=0.013). These effects in mice were observed at approximately 15 times (250 mg/kg/day) and 23 times (500 mg/kg/day) the HD of 80 mg, based on AUC. In another 2-year study in mice with doses up to 100 mg/kg/day (producing drug exposures approximately 2 times the HD of 80 mg, based on AUC), there were no drug-induced tumors.

No evidence of mutagenicity was observed in vitro, with or without rat-liver metabolic activation, in the following studies: microbial mutagen tests, using mutant strains of Salmonella typhimurium or Escherichia coli; a forward mutation assay in L5178Y TK +/− mouse lymphoma cells; a chromosomal aberration test in hamster cells; and a gene conversion assay using Saccharomyces cerevisiae. In addition, there was no evidence of mutagenicity in either a dominant lethal test in mice or a micronucleus test in mice.

In a fertility study in adult rats with daily doses up to 500 mg/kg, pravastatin did not produce any adverse effects on fertility or general reproductive performance. No adverse effects were seen in juvenile rats dosed with 5 mg/kg/day pravastatin (5 times plasma exposure at the maximum recommended human dose [MRHD] of 80 mg based on AUC) in a study of pravastatin administered from postnatal days (PND) 4 through 80 at 5, 15 and 45 mg/kg/day. A PND 4 rat is generally comparable to a 3rd trimester human fetus with regards to neurologic development/myelination. At ≥ 15 mg/kg/day (≥ 20 times the MRHD), decreased body-weight gain was observed during the pre-weaning period and slight thinning of the corpus callosum was observed at the end of the drug-free recovery period (PND 132). Thinning of the corpus callosum was not associated with any inflammatory or degenerative changes in the brain. Impacts on neurobehavioral and learning endpoints were detected only at very high exposures (43 times the MRHD). No thinning of the corpus callosum was observed in rats dosed with pravastatin for 3 months beginning on PND 35 at ≥ 250 mg/kg/day. PND 35 in a rat is approximately equivalent to an 8 to 12-year-old human child.

14 CLINICAL STUDIES

Prevention of Coronary Heart Disease

In the Pravastatin Primary Prevention Study (WOS), the effect of pravastatin on fatal and nonfatal CHD was assessed in 6,595 male patients 45 to 64 years of age, without a previous MI, and with LDL-C levels between 156 to 254 mg/dL. In this randomized, double-blind, placebo-controlled study, patients were treated with standard care, including dietary advice, and either pravastatin 40 mg daily (N=3,302) or placebo (N=3,293) and followed for a median duration of 4.8 years. Median (25th, 75th percentile) percent changes from baseline after 6 months of pravastatin treatment in Total-C, LDL-C, TG, and HDL-C were −20.3 (−26.9, −11.7), −27.7 (−36, −16.9), −9.1 (−27.6, 12.5), and 6.7 (−2.1, 15.6), respectively.

Pravastatin significantly reduced the rate of first coronary events (either CHD death or nonfatal MI) by 31% (248 events in the placebo group [CHD death=44, nonfatal MI=204] versus 174 events in the pravastatin group [CHD death=31, nonfatal MI=143], p=0.0001 [see figure below]). The risk reduction with pravastatin was similar across the age range studied and throughout the range of baseline LDL cholesterol levels.

Pravastatin also decreased the risk for undergoing myocardial revascularization procedures (coronary artery bypass graft [CABG] surgery or percutaneous transluminal coronary angioplasty [PTCA]) by 37% (80 vs 51 patients). Cardiovascular deaths were decreased by 32% (73 vs 50) and there was no increase in death from non-cardiovascular causes.

Secondary Prevention of Cardiovascular

Events In the LIPIDstudy, the effect of pravastatin, 40 mg daily, was assessed in 9,014 patients (7,498 men; 1,516 women; 3,514 patients ≥65 years; 782 patients with diabetes) who had experienced either an MI (5,754 patients) or had been hospitalized for unstable angina pectoris (3,260 patients) in the preceding 3 to 36 months. Patients in this multicenter, double-blind, placebo-controlled study participated for an average of 5.6 years (median of 5.9 years) and at randomization had Total-C between 114 and 563 mg/dL (mean 219 mg/dL), LDL-C between 46 and 274 mg/dL (mean 150 mg/dL), TG between 35 and 2,710 mg/dL (mean 160 mg/dL), and HDL-C between 1 and 103 mg/dL (mean 37 mg/dL). At baseline, 82% of patients were receiving aspirin and 76% were receiving antihypertensive medication. Treatment with pravastatin significantly reduced the risk for total mortality by reducing coronary death (see Table 7). The risk reduction due to treatment with pravastatin on CHD mortality was consistent regardless of age. Pravastatin significantly reduced the risk for total mortality (by reducing CHD death) and CHD events (CHD mortality or nonfatal MI) in patients who qualified with a history of either MI or hospitalization for unstable angina pectoris.

Table 7: LIPID - Primary and Secondary Endpoints

 | Number (%) of Subjects
Event |  | Pravastatin 40 mg (N=4,512) | Placebo (N=4,502) |  | Risk Reduction | p-value
Primary Endpoint
CHD mortality |  | 287 (6.4) | 373 (8.3) |  | 24% | 0.0004
Secondary Endpoints
Total mortality |  | 498 (11.0) | 633 (14.1) |  | 23% | <0.0001
CHD mortality or nonfatal MI |  | 557 (12.3) | 715 (15.9) |  | 24% | <0.0001
Myocardial revascularization procedures (CABG or PTCA) |  | 584 (12.9) | 706 (15.7) |  | 20% | <0.0001
Stroke
All-cause |  | 169 (3.7) | 204 (4.5) |  | 19% | 0.0477
Non-hemorrhagic |  | 154 (3.4) | 196 (4.4) |  | 23% | 0.0154
Cardiovascular mortality |  | 331 (7.3) | 433 (9.6) |  | 25% | <0.0001

In the CARE study, the effect of pravastatin, 40 mg daily, on CHD death and nonfatal MI was assessed in 4,159 patients (3,583 men and 576 women) who had experienced a MI in the preceding 3 to 20 months and who had normal (below the 75th percentile of the general population) plasma total cholesterol levels. Patients in this double-blind, placebo-controlled study participated for an average of 4.9 years and had a mean baseline Total-C of 209 mg/dL. LDL-C levels in this patient population ranged from 101 to 180 mg/dL (mean 139 mg/dL). At baseline, 84% of patients were receiving aspirin and 82% were taking antihypertensive medications. Median (25th, 75th percentile) percent changes from baseline after 6 months of pravastatin treatment in Total-C, LDL-C, TG, and HDL-C were −22 (−28.4, −14.9), −32.4 (−39.9, −23.7), −11 (−26.5, 8.6), and 5.1 (−2.9, 12.7), respectively. Treatment with pravastatin significantly reduced the rate of first recurrent coronary events (either CHD death or nonfatal MI), the risk of undergoing revascularization procedures (PTCA, CABG), and the risk for stroke or TIA (see Table 8).

Table 8: CARE - Primary and Secondary Endpoints

 | Number (%) of Subjects
Event |  | Pravastatin 40 mg (N=2,081) | Placebo (N=2,078) | Risk Reduction | p-value
Primary Endpoint
CHD mortality or nonfatal MIa |  | 212 (10.2) | 274 (13.2) | 24% | 0.003
Secondary Endpoints
Myocardial revascularization procedures (CABG or PTCA) |  | 294 (14.1) | 391 (18.8) | 27% | <0.001
Stroke or TIA |  | 93 (4.5) | 124 (6.0) | 26% | 0.029

a The risk reduction due to treatment with pravastatin was consistent in both sexes.

Primary Hyperlipidemia

In multicenter, double-blind, placebo-controlled studies of patients with primary hyperlipidemia, treatment with pravastatin in daily doses ranging from 10 to 40 mg consistently and significantly decreased Total-C, LDL-C, and TG (see Table 9).

In a pooled analysis of 2 multicenter, double-blind, placebo-controlled studies of patients with primary hyperlipidemia, treatment with pravastatin at a daily dose of 80 mg (N=277) significantly decreased Total-C, LDL-C, and TG. The 25th and 75th percentile changes from baseline in LDL-C for pravastatin 80 mg were −43% and −30%. The efficacy results of the individual studies were consistent with the pooled data (see Table 9).

Table 9: Primary Hyperlipidemia Trials: Dose Response of Pravastatin Once Daily Administration

Dose | Total-C | LDL-C | HDL-C | TG
Mean Percent Changes From Baseline After 8 Weeksa
Placebo (N=36) | -3% | -4% | +1% | -4%
10 mg (N=18) | -16% | -22% | +7% | -15%
20 mg (N=19) | -24% | -32% | +2% | -11%
40 mg (N=18) | -25% | -34% | +12% | -24%
Mean Percent Changes From Baseline After 6 Weeksb
Placebo (N=162) | 0% | -1% | -1% | +1%
80 mg (N=277) | -27% | -37% | +3% | -19%

a A multicenter, double-blind, placebo-controlled study.

b Pooled analysis of 2 multicenter, double-blind, placebo-controlled studies.

Hypertriglyceridemia

The response to pravastatin in patients with hypertriglyceridemia (baseline TG >200 mg/dL and LDL-C <160 mg/dL) was evaluated in a subset of 429 patients from the CARE study. For pravastatin-treated subjects, the median (min, max) baseline TG level was 246 (200.5, 349.5) mg/dL (see Table 10).

Table 10: Patients with Hypertriglyceridemia Median (25th, 75th percentile) % Change from Baseline

 | Pravastatin 40 mg (N=429) | Placebo (N=430)
TG | -21.1 (-34.8, 1.3) | -6.3 (-23.1, 18.3)
Total-C | -22.1 (-27.1, -14.8) | 0.2 (-6.9, 6.8)
LDL-C | -31.7 (-39.6, -21.5) | 0.7 (-9.0, 10.0)
HDL-C | 7.4 (-1.2, 17.7) | 2.8 (-5.7, 11.7)
Non-HDL-C | -27.2 (-34.0, -18.5) | -0.8 (-8.2, 7.0)

Dysbetalipoproteinemia

The response to pravastatin in two double-blind crossover studies of 46 patients with genotype E2/E2 and dysbetalipoproteinemia is shown in Table 11.

Table 11: Patients with Dysbetalipoproteinemia Median (min, max) % Change from Baseline

 | Median (min, max) at Baseline (mg/dL) | Median % Change (min, max) Pravastatin 40 mg (N=20)
Study 1
Total-C | 386.5 (245.0, 672.0) | -32.7 (-58.5, 4.6)
TG | 443.0 (275.0, 1,299.0) | -23.7 (-68.5, 44.7)
VLDL-Ca | 206.5 (110.0, 379.0) | -43.8 (-73.1, -14.3)
LDL-Ca | 117.5 (80.0, 170.0) | -40.8 (-63.7, 4.6)
HDL-C | 30.0 (18.0, 88.0) | 6.4 (-45.0, 105.6)
Non-HDL-C | 344.5 (215.0, 646.0) | -36.7 (-66.3, 5.8)
a N=14
 | Median (min, max) at Baseline (mg/dL) | Median % Change (min, max) Pravastatin 40 mg (N=26)
Study 2
Total-C | 340.3 (230.1, 448.6) | -31.4 (-54.5, -13.0)
TG | 343.2 (212.6, 845.9) | -11.9 (-56.5, 44.8)
VLDL-C | 145.0 (71.5, 309.4) | -35.7 (-74.7, 19.1)
LDL-C | 128.6 (63.8, 177.9) | -30.3 (-52.2, 13.5)
HDL-C | 38.7 (27.1, 58.0) | 5.0 (-17.7, 66.7)
Non-HDL-C | 295.8 (195.3, 421.5) | -35.5 (-81.0, -13.5)

HeFH in Pediatric Patients Aged 8 Years and Above

A double-blind, placebo-controlled study in 214 pediatric patients (100 males and 114 females) with heterozygous familial hypercholesterolemia (HeFH), aged 8 to 18 years was conducted for 2 years. The pediatric patients aged 8 to 13 years were randomized to placebo (N=63) or 20 mg of pravastatin daily (N=65) and the pediatric patients aged 14 to 18 years were randomized to placebo (N=45) or 40 mg of pravastatin daily (N=41). Inclusion in the study required an LDL-C level >95th percentile for age and sex and one parent with either a clinical or molecular diagnosis of familial hypercholesterolemia. The mean baseline LDL-C value was 239 mg/dL and 237 mg/dL in the pravastatin (range: 151 to 405 mg/dL) and placebo (range: 154 to 375 mg/dL) groups, respectively.

Pravastatin significantly decreased plasma levels of LDL-C, Total-C, and ApoB in both pediatric age groups (see Table 12). The effect of pravastatin treatment in the 2 age groups was similar.

Table 12: Lipid-Lowering Effects of Pravastatin in Pediatric Patients with Heterozygous Familial Hypercholesterolemia: Least-Squares Mean % Change from Baseline at Month 24 (Last Observation Carried Forward: Intent-to-Treat)a

 | Pravastatin 20 mg (Aged 8 to 13 years) N=65 | Pravastatin 40 mg (Aged 14 to 18 years) N=41 | Combined Pravastatin (Aged 8 to 18 years) N=106 | Combined Placebo (Aged 8 to 18 years) N=108 | 95% CI of the Difference Between Combined Pravastatin and Placebo
LDL-C | -26.04b | -21.07b | -24.07b | -1.52 | (-26.74, -18.86)
TC | -20.75b | -13.08b | -17.72b | -0.65 | (-20.40, -13.83)
HDL-C | 1.04 | 13.71 | 5.97 | 3.13 | (-1.71, 7.43)
TG | -9.58 | -0.30 | -5.88 | -3.27 | (-13.95, 10.01)
ApoB (N) | -23.16b (61) | -18.08b (39) | -21.11b (100) | -0.97 (106) | (-24.29, -16.18)

a The above least-squares mean values were calculated based on log-transformed lipid values.

b Significant at p≤0.0001 when compared with placebo.

The mean achieved LDL-C was 186 mg/dL (range: 67 to 363 mg/dL) in the pravastatin group k to 236 mg/dL (range: 105 to 438 mg/dL) in the placebo group.

16 HOW SUPPLIED/STORAGE AND HANDLING

16.1 How Supplied

Pravastatin Sodium Tablets, USP 10 mg are available for oral administration as light pink, round, unscored tablets, imprinted “APO” on one side and “PRA” over “10” on the other side. They are supplied as follows:

Blistercards of 30 (NDC 0615-8618-39)

Pravastatin Sodium Tablets, USP 20 mg are available for oral administration as off-white to light yellow, round, unscored tablets, imprinted “APO” on one side and “PRA” over “20” on the other side. They are supplied as follows:

Blistercards of 30 (NDC 0615-8619-39)
Blistercards of 15 (NDC 0615-8619-05)

Pravastatin Sodium Tablets, USP 40 mg are available for oral administration as light green, round, unscored tablets, imprinted “APO” on one side and “PRA” over “40” on the other side. They are supplied as follows:

Blistercards of 30 (NDC 0615-8620-39)
Blistercards of 15 (NDC 0615-8620-05)

Pravastatin Sodium Tablets, USP 80 mg are available for oral administration as off-white to light yellow, round, unscored tablets, imprinted "APO" on one side and "PRA" over "80" on the other side. They are supplied as follows:

Blistercards of 30 (NDC 0615-8621-39)

Store at 20°C to 25°C (68°F to 77°F); excursions permitted to 15°C to 30°C (59°F to 86°F). [See USP Controlled Room Temperature]. Dispense in a tight, light-resistant container [see USP]. Protect from light and moisture.

17 PATIENT COUNSELING INFORMATION

Myopathy and Rhabdomyolysis

Advise patients that pravastatin sodium tablets may cause myopathy and rhabdomyolysis. Inform patients that the risk is increased when taking certain types of medication and they should discuss all medication, both prescription and over the counter, with their healthcare provider. Instruct patients to promptly report any unexplained muscle pain, tenderness or weakness particularly if accompanied by malaise or fever [see Warnings and Precautions (5.1), Drug Interactions (7.1)].

Hepatic Dysfunction

Inform patients that pravastatin sodium tablets may cause liver enzyme elevations and possibly liver failure. Advise patients to promptly report fatigue, anorexia, right upper abdominal discomfort, dark urine or jaundice [see Warnings and Precautions (5.3)].

Increases in HbA1c and Fasting Serum Glucose Levels

Inform patients that increases in HbA1c and fasting serum glucose levels may occur with pravastatin sodium tablets. Encourage patients to optimize lifestyle measures, including regular exercise, maintaining a healthy body weight, and making healthy food choices [see Warnings and Precautions (5.4)].

Pregnancy

Advise pregnant patients and patients who may become pregnant of the potential risk to a fetus. Advise patients to inform their healthcare provider of a known or suspected pregnancy to discuss if pravastatin sodium tablets should be discontinued [see Use in Specific Populations (8.1)].

Lactation

Advise patients that breastfeeding is not recommended during treatment with pravastatin sodium tablets [see Use in Specific Populations (8.2)].

APOTEX INC.
PRAVASTATIN SODIUM TABLETS, USP
10 mg, 20 mg, 40 mg and 80 mg

Manufactured by Manufactured for

Apotex Inc. Apotex Corp.

Toronto, Ontario Weston, Florida

Canada M9L 1T9 USA, 33326

Rev. 14